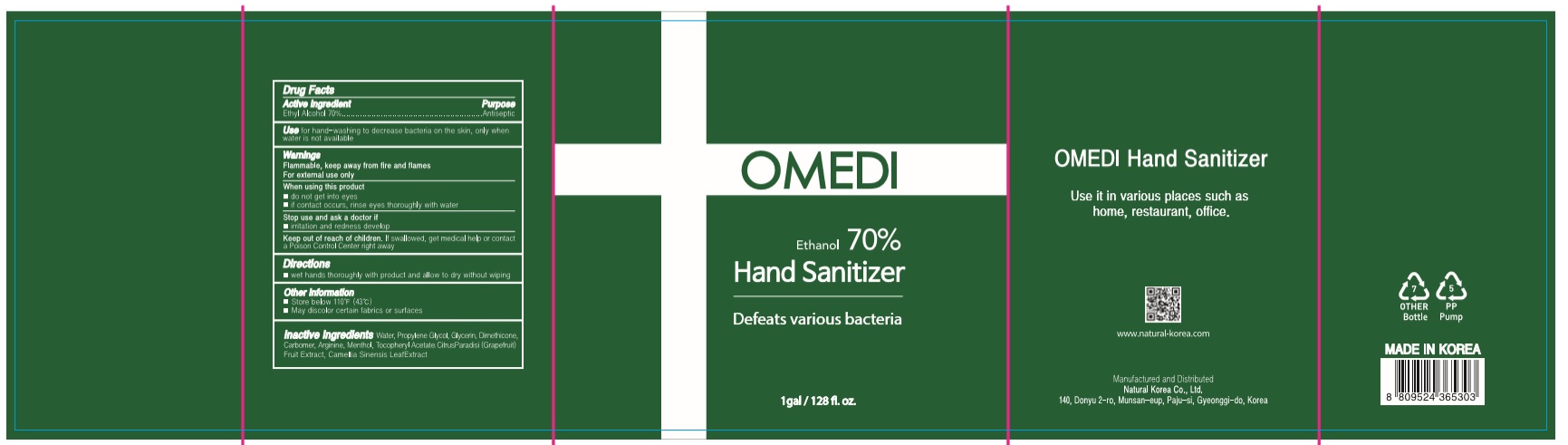 DRUG LABEL: OMEDI Hand Sanitizer
NDC: 74646-3785 | Form: GEL
Manufacturer: Natural Korea Co., Ltd.
Category: otc | Type: HUMAN OTC DRUG LABEL
Date: 20200714

ACTIVE INGREDIENTS: ALCOHOL 2649.5 mL/3785 mL
INACTIVE INGREDIENTS: ALPHA-TOCOPHEROL ACETATE; MENTHOL; PROPYLENE GLYCOL; GLYCERIN; DIMETHICONE; GREEN TEA LEAF; WATER; CARBOMER HOMOPOLYMER, UNSPECIFIED TYPE; ARGININE; GRAPEFRUIT

[OMEDI HAND SANITIZER] 1 Gallon(128 fl. oz. 3785 mL) : 74646-3785-1